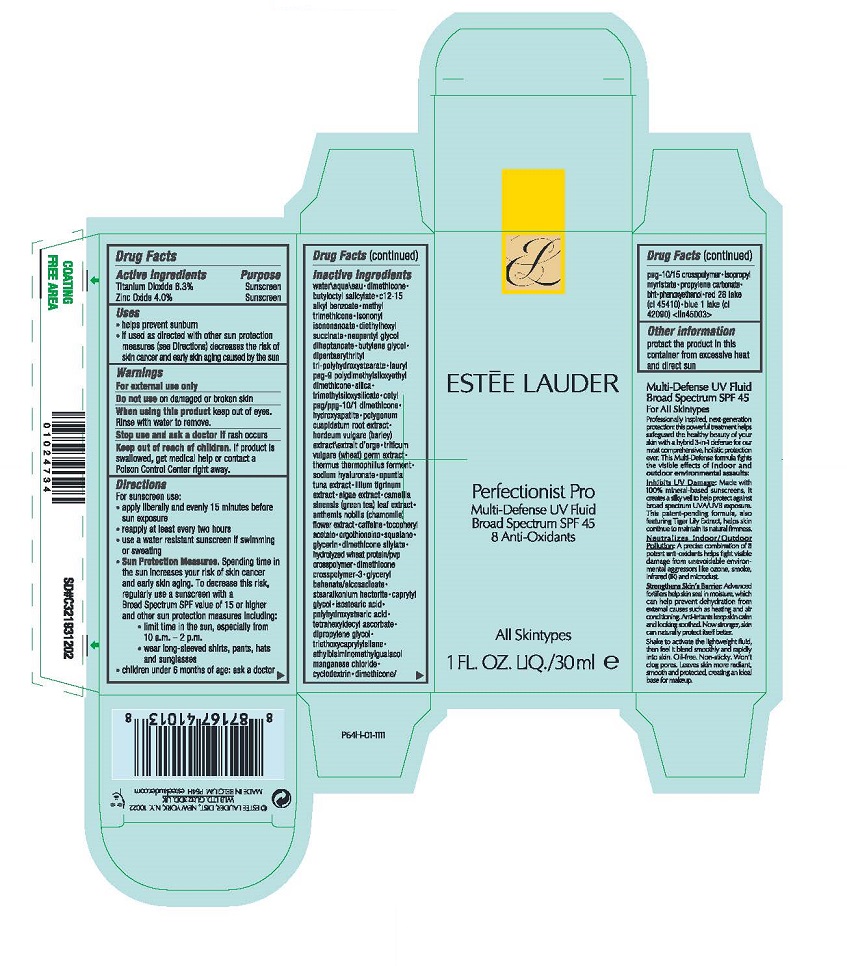 DRUG LABEL: PERFECTIONIST PRO MULTI-DEFENSE UV FLUID BROAD SPRECTRUM SPF 45
NDC: 11559-050 | Form: LOTION
Manufacturer: ESTEE LAUDER INC
Category: otc | Type: HUMAN OTC DRUG LABEL
Date: 20231026

ACTIVE INGREDIENTS: TITANIUM DIOXIDE 63 mg/1 mL; ZINC OXIDE 40 mg/1 mL
INACTIVE INGREDIENTS: DIMETHICONE; WATER; BUTYLOCTYL SALICYLATE; ALKYL (C12-15) BENZOATE; METHYL TRIMETHICONE; ISONONYL ISONONANOATE; DIETHYLHEXYL SUCCINATE; NEOPENTYL GLYCOL DIHEPTANOATE; BUTYLENE GLYCOL; DIPENTAERYTHRITYL TRI-POLYHYDROXYSTEARATE; LAURYL PEG-9 POLYDIMETHYLSILOXYETHYL DIMETHICONE; SILICON DIOXIDE; TRIBASIC CALCIUM PHOSPHATE; BARLEY; WHEAT; THERMUS THERMOPHILUS LYSATE; HYALURONATE SODIUM; GREEN TEA LEAF; CHAMOMILE; CAFFEINE; .ALPHA.-TOCOPHEROL ACETATE; ERGOTHIONEINE; SQUALANE; GLYCERIN; GLYCERYL BEHENATE/EICOSADIOATE; STEARALKONIUM HECTORITE; CAPRYLYL GLYCOL; ISOSTEARIC ACID; TETRAHEXYLDECYL ASCORBATE; DIPROPYLENE GLYCOL; TRIETHOXYCAPRYLYLSILANE; ETHYLBISIMINOMETHYLGUAIACOL MANGANESE CHLORIDE; ISOPROPYL MYRISTATE; PROPYLENE CARBONATE; BUTYLATED HYDROXYTOLUENE; PHENOXYETHANOL; D&C RED NO. 28; ALUMINUM OXIDE; FD&C BLUE NO. 1

PERFECTIONIST PRO MULTI-DEFENSE UV FLUID BROAD SPRECTRUM SPF 45

Drug Facts

ACTIVE INGREDIENT

Active ingredients | Purpose
Titanium Dioxide 6.3% | Sunscreen
Zinc Oxide 4.0% | Sunscreen

Uses

- helps prevent sunburn
- if used as directed with other sun protection measures (see Directions) decreases the risk of skin cancer and early skin aging caused by the sun

Warnings

For external use only

Do not use on damaged or broken skin

When using this product keep out of eyes. Rinse with water to remove.

Stop use and ask a doctor if rash occurs

Keep out of reach of children. If product is swallowed, get medical help or contact a Poison Control Center right away.

Directions

For sunscreen use:

- apply liberally and evenly 15 minutes before sun exposure
- reapply at least every two hours
- use a water resistant sunscreen if swimming or sweating
- Sun Protection Measures. Spending time in the sun increases your risk of skin cancer and early skin aging. To decrease this risk, regularly use a sunscreen with a Broad Spectrum SPF value of 15 or higher and other sun protection measures including:
  - limit time in the sun, especially from 10 a.m. – 2 p.m.
  - wear long-sleeved shirts, pants, hats and sunglasses
- children under 6 months of age: ask a doctor

Inactive ingredients

water\aqua\eau • dimethicone • butyloctyl salicylate • c12-15 alkyl benzoate • methyl trimethicone • isononyl isononanoate • diethylhexyl succinate • neopentyl glycol diheptanoate • butylene glycol • dipentaerythrityl tri-polyhydroxystearate • lauryl peg-9 polydimethylsiloxyethyl dimethicone • silica • trimethylsiloxysilicate • cetyl peg/ppg-10/1 dimethicone • hydroxyapatite • polygonum cuspidatum root extract • hordeum vulgare (barley) extract\extrait d'orge • triticum vulgare (wheat) germ extract • thermus thermophillus ferment • sodium hyaluronate • opuntia tuna extract • lilium tigrinum extract • algae extract • camellia sinensis (green tea) leaf extract • anthemis nobilis (chamomile) flower extract • caffeine • tocopheryl acetate • ergothioneine • squalane • glycerin • dimethicone silylate • hydrolyzed wheat protein/pvp crosspolymer • dimethicone crosspolymer-3 • glyceryl behenate/eicosadioate • stearalkonium hectorite • caprylyl glycol • isostearic acid • polyhydroxystearic acid • tetrahexyldecyl ascorbate • dipropylene glycol • triethoxycaprylylsilane • ethylbisiminomethylguaiacol manganese chloride • cyclodextrin • dimethicone/peg-10/15 crosspolymer • isopropyl myristate • propylene carbonate • bht • phenoxyethanol • red 28 lake (ci 45410) • blue 1 lake (ci 42090) <iln45003>

Other information

protect the product in this container from excessive heat and direct sun

PRINCIPAL DISPLAY PANEL - 30 ml Container Carton

ESTĒE LAUDER

Perfectionist Pro

Multi-Defense UV Fluid
Broad Spectrum SPF 45
8 Anti-Oxidants

All Skintypes

1 FL. OZ. LIQ./30 ml e